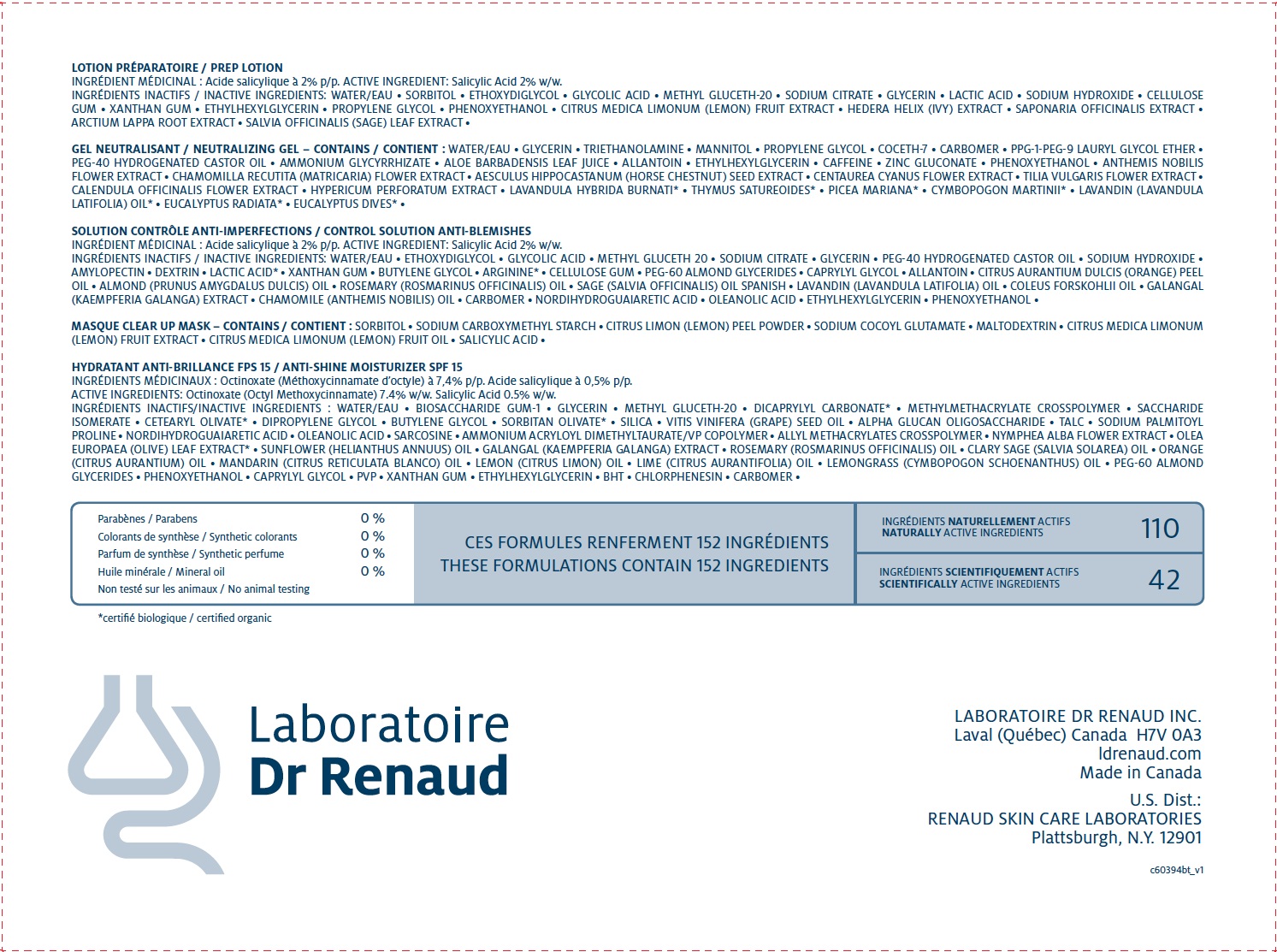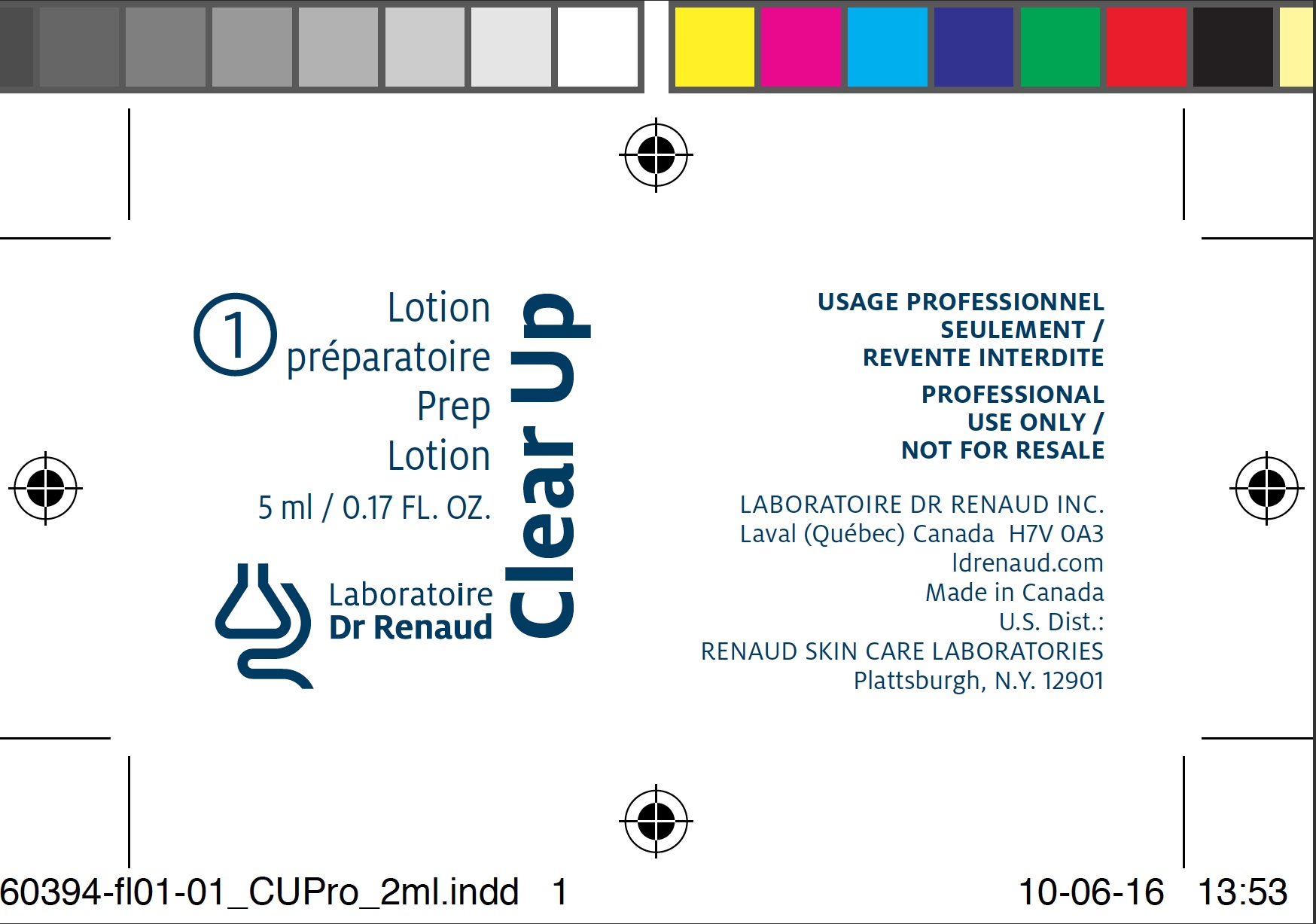 DRUG LABEL: CLEAR UP Prep
NDC: 62499-395 | Form: GEL
Manufacturer: Laboratoire Dr. Renaud
Category: otc | Type: HUMAN OTC DRUG LABEL
Date: 20100701

ACTIVE INGREDIENTS: SALICYLIC ACID 2 g/100 g
INACTIVE INGREDIENTS: WATER; SORBITOL; DIETHYLENE GLYCOL MONOETHYL ETHER; GLYCOLIC ACID; METHYL GLUCETH-20; SODIUM CITRATE; GLYCERIN; LACTIC ACID; SODIUM HYDROXIDE; PROPYLENE GLYCOL; PHENOXYETHANOL; CARBOXYMETHYLCELLULOSE SODIUM; XANTHAN GUM; ETHYLHEXYLGLYCERIN; LEMON OIL; SAPONARIA OFFICINALIS ROOT; ARCTIUM LAPPA ROOT; SAGE OIL

Drug Facts

ACTIVE INGREDIENT

Salicylic Acid 2% w/w.

INACTIVE INGREDIENTS

WATER • SORBITOL • ETHOXYDIGLYCOL • GLYCOLIC ACID • METHYL GLUCETH-20 • SODIUM CITRATE • GLYCERIN • LACTIC ACID • SODIUM HYDROXIDE • CELLULOSE GUM • XANTHAN GUM • ETHYLHEXYLGLYCERIN • PROPYLENE GLYCOL • PHENOXYETHANOL • CITRUS MEDICA LIMONUM (LEMON) FRUIT EXTRACT • HEDERA HELIX (IVY) EXTRACT • SAPONARIA OFFICINALIS EXTRACT •
ARCTIUM LAPPA ROOT EXTRACT • SALVIA OFFICINALIS (SAGE) LEAF EXTRACT •

DIRCETIONS

Cover the eyes with cotton pads soaked in Blue Water. With the fingertips, apply evenly to the face and neck CLEAR UP Prep Lotion, making sure to avoid the lips.

Application: 2-3 minutes | Pause: 7-8 minutes

WARNINGS

Enter section text here

image of carton label
image of tube 5ml label

INDICATIONS AND USAGE

Enter section text here

Keep out of reach of children.

PURPOSE

Enter section text here